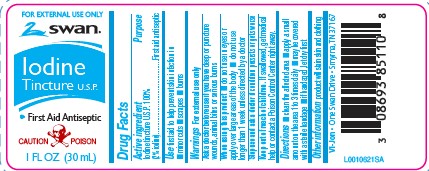 DRUG LABEL: Iodine
NDC: 11344-880 | Form: LIQUID
Manufacturer: Consumer Product Partners, LLC
Category: otc | Type: HUMAN OTC DRUG LABEL
Date: 20250625

ACTIVE INGREDIENTS: IODINE 20 mg/1 mL
INACTIVE INGREDIENTS: ALCOHOL; WATER; SODIUM IODIDE

Swan 088.000/088AA
Iodine Tincture U.S.P.

Active Ingredient

Iodine tincture U.S.P. 100%

(2% Iodine)

Purpose

First aid antiseptic

Use

First aid to help prevent skin infection in

- minor cuts
- scrapes
- burns

Warnings

For external use only

Ask a doctor if you have

deep or puncture wounds, animal bites or serious burns

When using this product

- do not use in eyes or apply over large areas of the body
- do not use longer than 1 week unless directed by a doctor

Stop use and ask a doctor if

condition persists or gets worse

Keep out of reach of children.

If swallowed, get medical help or contact a Poison Control Center right away.

Directions

- clean the affected area
- apply a small amount on the area 1 to 3 times daily
- may be covered with a sterile bandage
- if bandaged, let dry first

Other information

product will stain skin and clothing

ADVERSE REACTION

Vi-Jon One Swan Drive, Smyrna, TN 37167

Inactive ingredients

alcohol (47% v/v), purified water, sodium iodide

Principal display panel

FOR EXTERNAL USE ONLY

Swan®

Iodine Tincture U.S.P.

- First Aid Antiseptic

CAUTION POISON

1 FL OZ (30 mL)